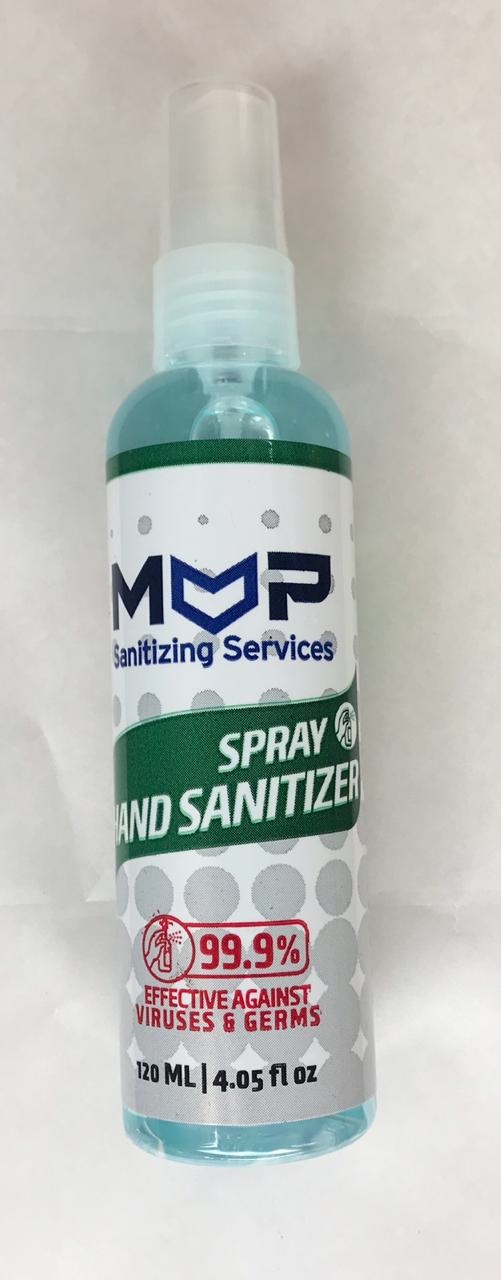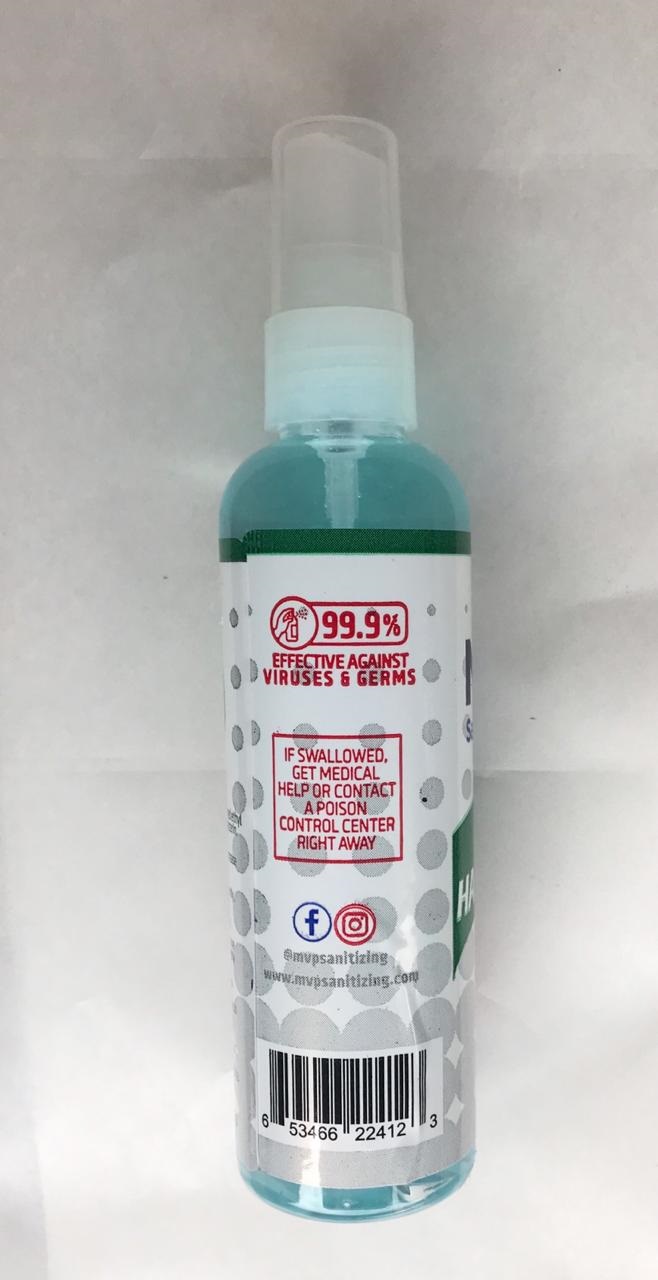 DRUG LABEL: Hand Sanitizer
NDC: 76947-198 | Form: SPRAY
Manufacturer: SNS Distribution LLC
Category: otc | Type: HUMAN OTC DRUG LABEL
Date: 20200508

ACTIVE INGREDIENTS: ALCOHOL 70 mL/70 mL
INACTIVE INGREDIENTS: HYDROGEN PEROXIDE; WATER; GLYCERIN

Hand Sanitizer

DOSAGE AND ADMINISTRATION

Directions: Spray on palm, rub hands together.

Warnings: For external use only, flammable.

keep away from fire or flame

INACTIVE INGREDIENT

Water,Glycerin,Hydrogen peroxide

INDICATIONS AND USAGE

Uses: for hand washing to decrease bacteria on skin.

Keep out of reach of children.

Do not use near eyes, in case of contact rinse eyes thorouhly with water.

KEEP OUT OF REACH OF CHILDREN

If swallowed,get medical help or contact a Poison Control Center right away.

PURPOSE

Antiseptic

ACTIVE INGREDIENT

Alcohol 70%

Alcohol 70%. Purpose Anticeptic

120 ml NDC 76947-198-20